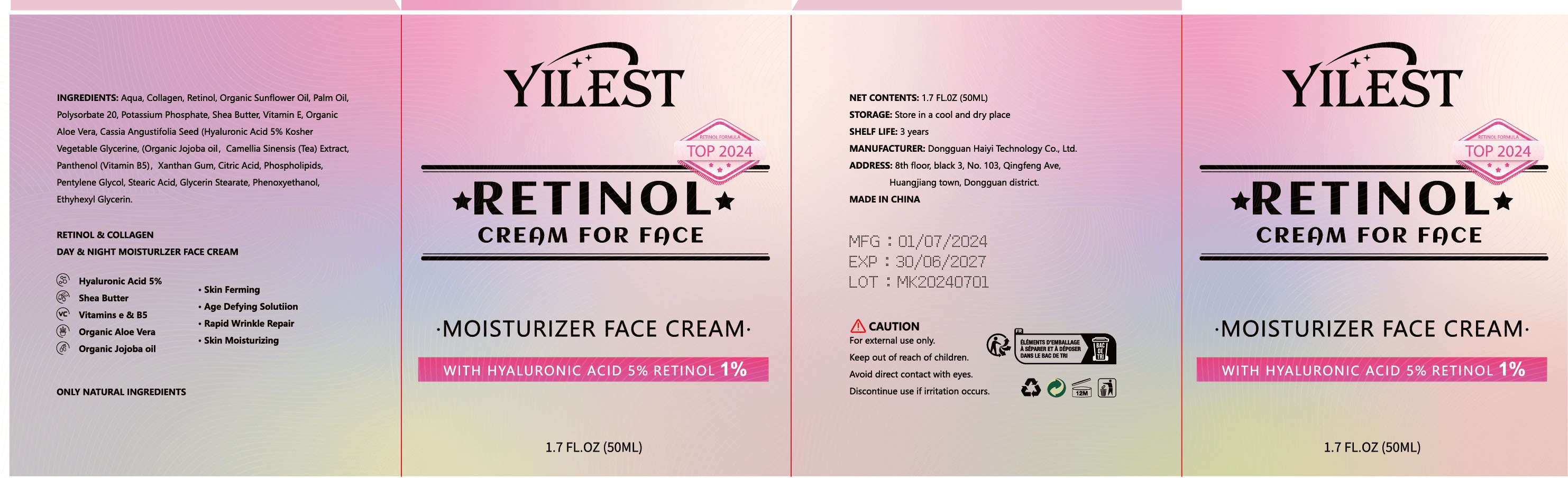 DRUG LABEL: Retinol cream for face moisturizer face cream
NDC: 84732-081 | Form: CREAM
Manufacturer: Dongguan Haiyi Technology Co.,Ltd.
Category: otc | Type: HUMAN OTC DRUG LABEL
Date: 20241103

ACTIVE INGREDIENTS: RETINOL 1 mg/50 mL
INACTIVE INGREDIENTS: ALOE VERA LEAF; CASSIA ANGUSTIFOLIA SEED EXTRACT; WATER; EQUINE COLLAGEN; SHEA BUTTER; POLYSORBATE 20; VITAMIN E POLYETHYLENE GLYCOL SUCCINATE; SUNFLOWER OIL; POTASSIUM PHOSPHATE

Active ingredient

Retinol

Inactive ingredient

Aqua, Collagen, Organic Sunflower Oil, Palm Oil,Polysorbate 20, Potassium Phosphate, Shea Butter, Vitamin E, OrganicAloe Vera, Cassia Angustifolia Seed (Hyaluronic Acid 5% KosherVegetable Glycerine, (Organic Jojoba oil, Camellia Sinensis (Tea) Extract,Panthenol (Vitamin B5),Xanthan Gum, Citric Acid, Phospholipids,Pentylene Glycol, Stearic Acid, Glycerin Stearate, Phenoxyethanol,Ethyhexyl Glycerin.

Purpose section

Smooths and brightens the complexion for a glamorous glow.

Warning

1).For external use only, avoid directcontact with eyes, lf you feel any
discomfort, stop using itand wash it with plenty of water. In severe cases,
pleaseseek medical attention in time.
2). Not allowed to be used ondamaged skin,

stop use

This product may cause allergic reactions in asmall number of people.
lf youexperience any discomfort,please stop using it immediately.

not use

Not suitable for use by children, pregnantor breast feeding people.

OUT OF CHILDREN

KEEP THE PRODUCT OUT OF REACH OF CHILDREN to

HOW TO USE

1. Cleanse and Tone: Start with clean skin, using a cleanser and toner suited to your skin type.
2. Use a Pea-Sized Amount: Scoop a small amount of cream (about a pea-sized amount) and warm it between your fingers to help with absorption.
3. Apply Gently: Dot the cream onto your forehead, cheeks, nose, and chin. Spread it evenly using gentle, upward and outward motions. Avoid the eye area unless the cream is specifically formulated for it.
4. Massage In: Lightly massage the cream into the skin for better absorption and circulation.
5. Wait Before Layering: Allow a few minutes for the cream to absorb before applying any other products, such as makeup or sunscreen.

Dosage

take an appropriateamount,Use 2-3 times a week